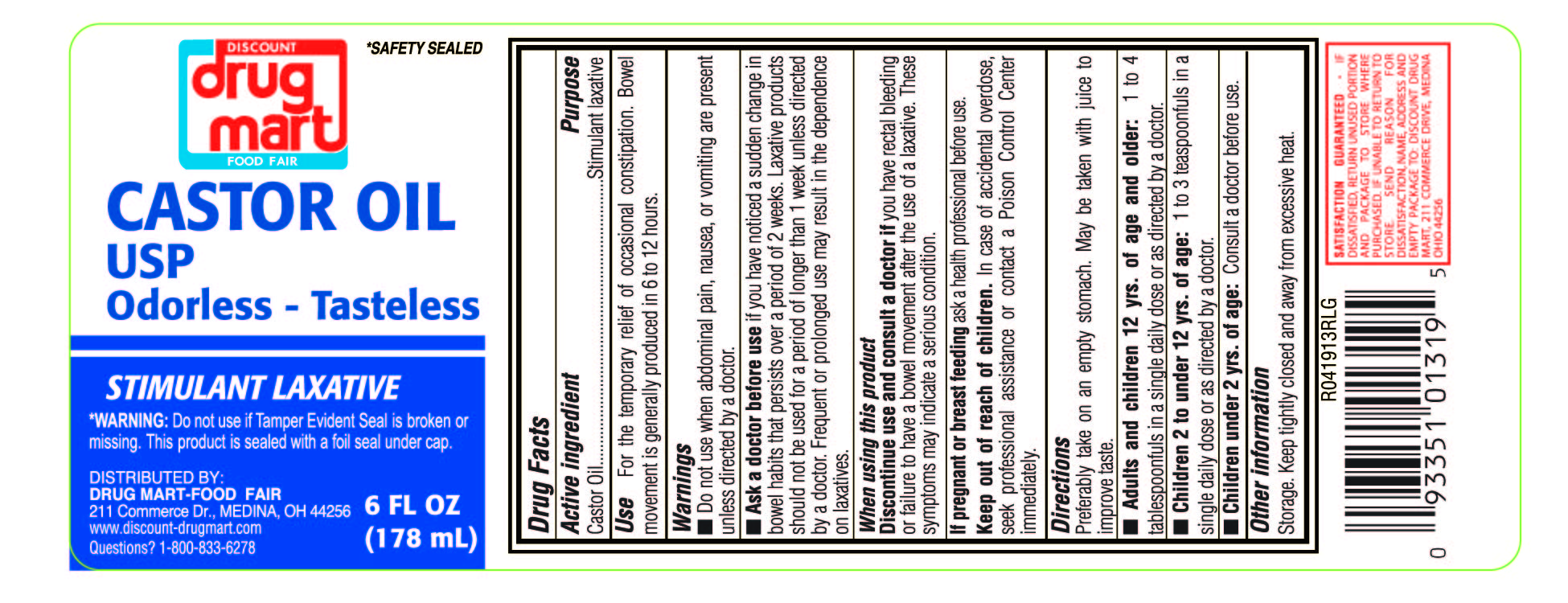 DRUG LABEL: DDM Castor Oil
NDC: 53943-515 | Form: LIQUID
Manufacturer: Discount Drug Mart
Category: otc | Type: HUMAN OTC DRUG LABEL
Date: 20251219

ACTIVE INGREDIENTS: CASTOR OIL 1 mg/1 mL
INACTIVE INGREDIENTS: WATER

DDM Castor Oil

Drug Facts

Active Ingredient

Castor Oil

Purpose

Stimulant Laxative

Use

For the temporary relief of occasional constipation. Bowel movement is generally produced in 6 to 12 hours.

Warings

Do not use when abdominal pain, nausea, or vomiting are present unless directed by a doctor.

Ask a doctor before use

if you have noticed a sudden change in bowel habits that persists over a period of 2 weeks. Laxative products should not be used for a period of longer than 1 week unless directed by a doctor. Frequent or prolonged use may result in the dependence on laxatives.

When using this product

Discontinue use and consult a doctor if you have rectal bleeding or failure to have a bowel movement after the use of a laxative. Thee symptoms may indicate a serious condition.

If pregnant or breast feeding

ask a health professional before use

Keep out of reach of children.

In case of accidental overdose, seek profssional assistance or contact a Poison Control Center immediately.

Directions

Preferably take on an empty stomach. May be taken with juice to improve taste.

Adults and children 12 yrs. of age and older: 1 to 4 tablesponfuls in a single daily dose or as directed by a doctor.

Children 2 to under 12 yrs. of age: 1 to 3 teaspoonfuls in a single dose or as directed by a doctor.

Children under 2 yrs. of age: Consult a doctor before use.

WARNINGS:

Do not use if Taper Evident Seal is broken or missing. This product is sealed with either a shrink band around cap imprinted "Sealed For your Protection" or foil seal under cap.

Other Information

storage. Keep tightly closed and away from excessive heat.

Inactive Ingredient

None